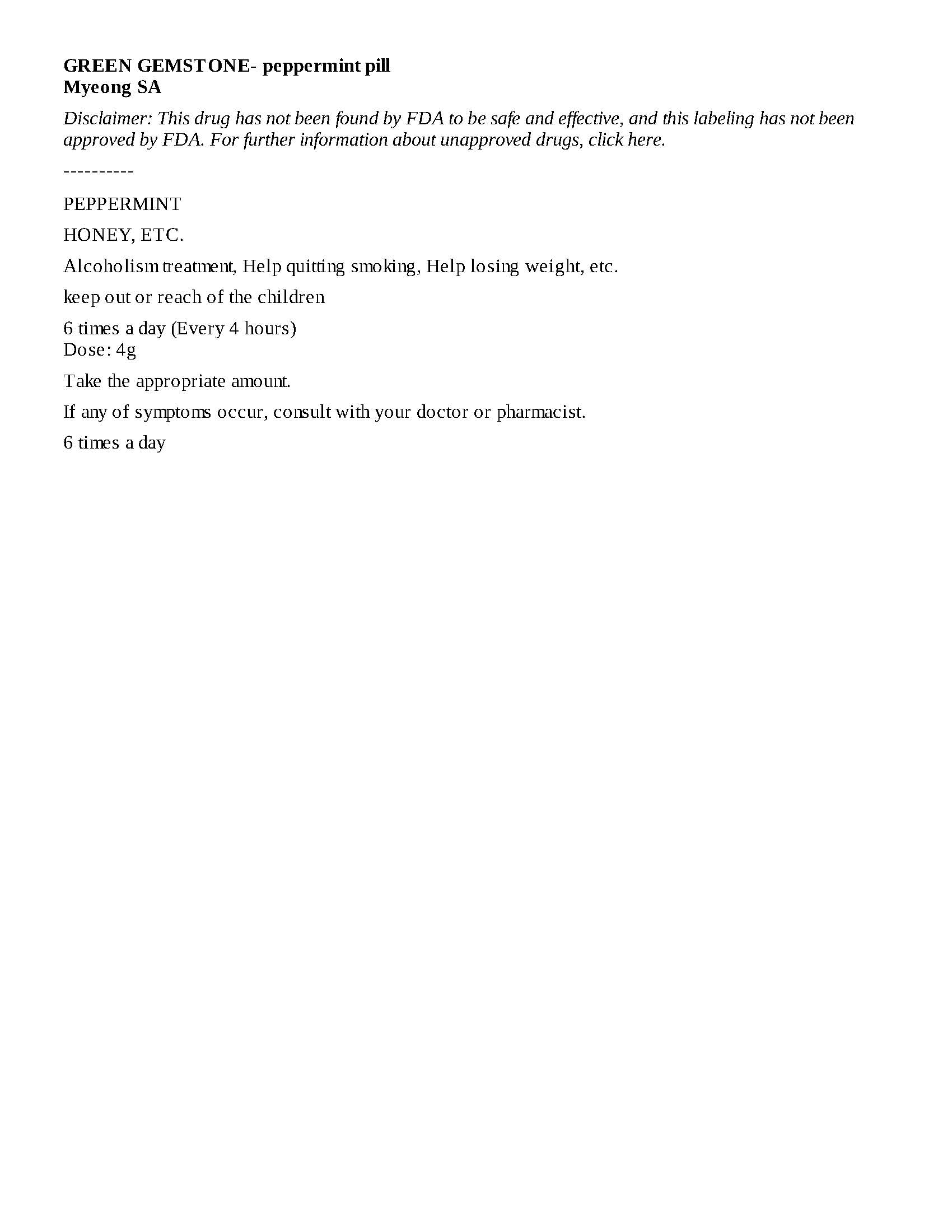 DRUG LABEL: GREEN GEMSTONE
NDC: 71960-0002 | Form: PILL
Manufacturer: Myeong SA
Category: otc | Type: HUMAN OTC DRUG LABEL
Date: 20200116

ACTIVE INGREDIENTS: PEPPERMINT 20 g/100 g
INACTIVE INGREDIENTS: HONEY

ACTIVE INGREDIENT

PEPPERMINT

INACTIVE INGREDIENT

HONEY, ETC.

PURPOSE

Alcoholism treatment, Help quitting smoking, Help losing weight, etc.

keep out or reach of the children

INDICATIONS AND USAGE

6 times a day (Every 4 hours)
Dose: 4g

WARNINGS

Take the appropriate amount.

If any of symptoms occur, consult with your doctor or pharmacist.

DOSAGE AND ADMINISTRATION

6 times a day